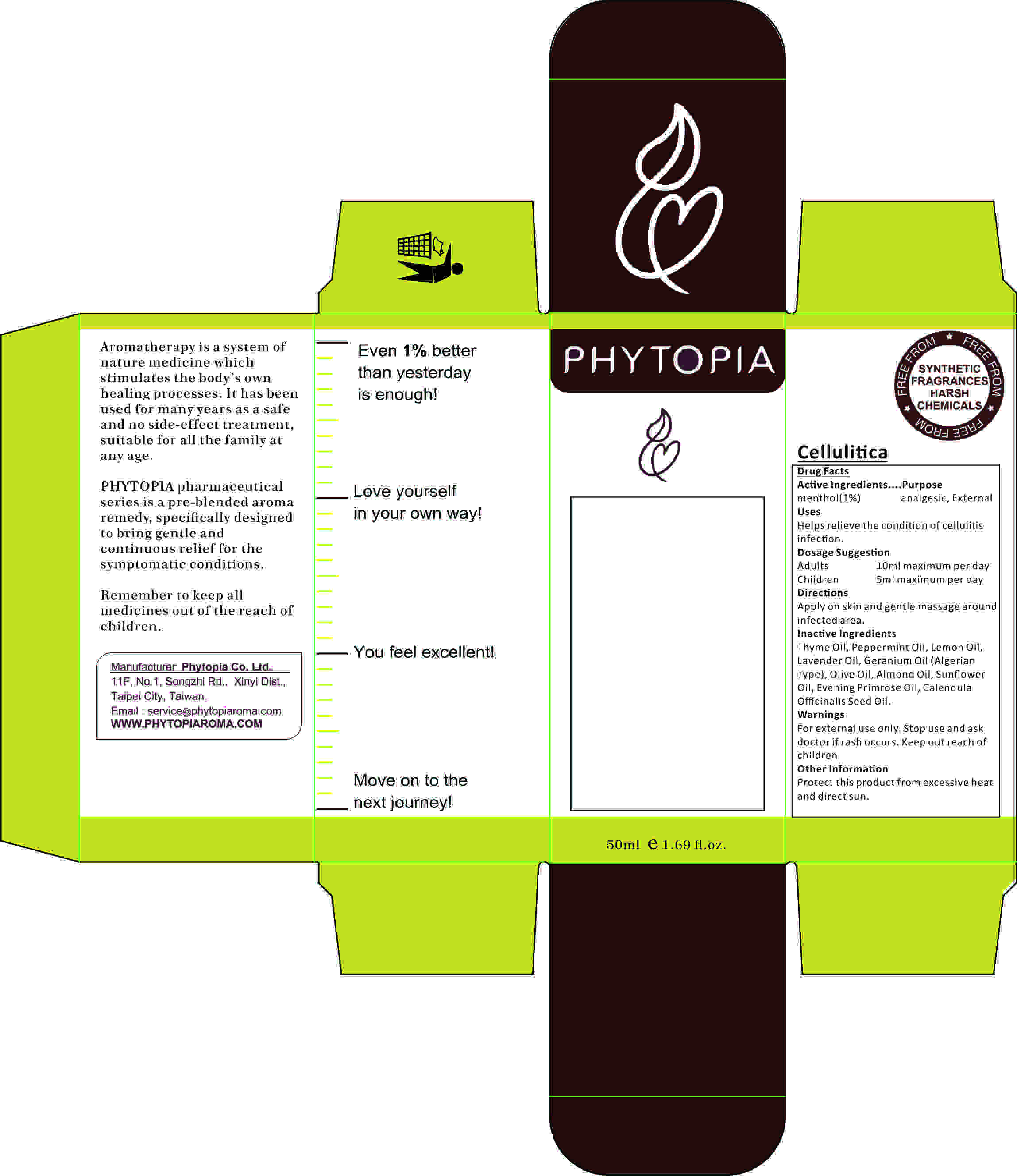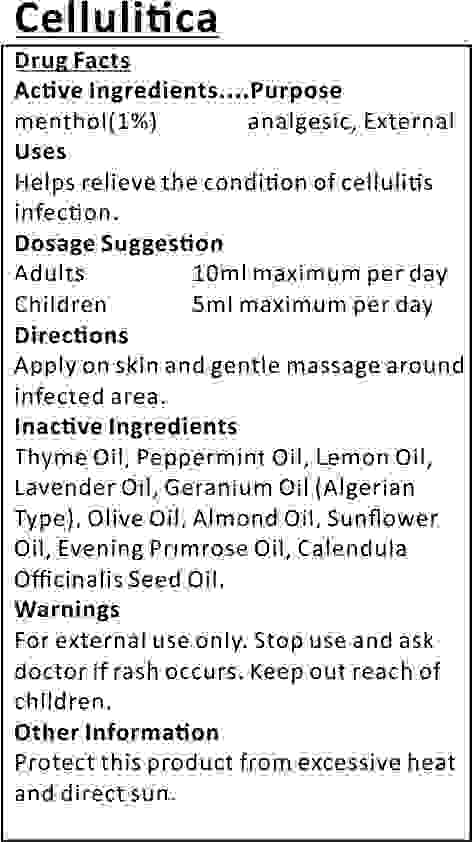 DRUG LABEL: menthol
NDC: 70470-1011 | Form: OIL
Manufacturer: PHYTOPIA CO., LTD.
Category: otc | Type: HUMAN OTC DRUG LABEL
Date: 20160217
DEA Schedule: CV

ACTIVE INGREDIENTS: MENTHOL 0.5 mg/50 mL
INACTIVE INGREDIENTS: CALENDULA OFFICINALIS SEED OIL 4.5 mL/50 mL; ALMOND OIL 12 mL/50 mL; PHENOL 3 mg/50 mL; OLIVE OIL 21 mL/50 mL; LEMON OIL 1 mL/50 mL; GERANIUM OIL, ALGERIAN TYPE 1 mL/50 mL; LAVENDER OIL 1 mL/50 mL; EVENING PRIMROSE OIL 6 mL/50 mL

active ingredient

menthol(1%) analgesic, External
Uses

Uses

Helps relieve the condition of cellulitis infection.

Dosage Suggestion

Adults 10ml maximum per day, Children 5ml maximum per day

Directions

Apply on skin and gentle massage around infected area.

Inactive Ingredient

Thyme Oil, Peppermint Oil, Lemon Oil, Lavender Oil, Geranium Oil (Algerian Type), Olive Oil, Almond Oil, Sunflower Oil, Evening Primrose Oil, Calendula Officinalis Seed Oil.

Warning

- For external use only.
- Stop use and ask doctor if rash occurs.
- Keep out reach of children.

Warning

Keep out reach of children.

Other Information

Protect this product from excessive heat and direct sun.